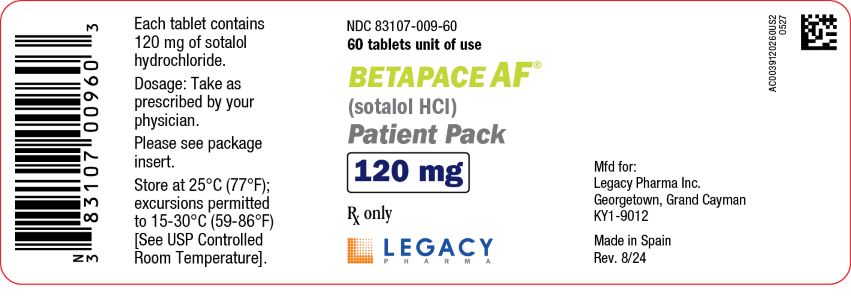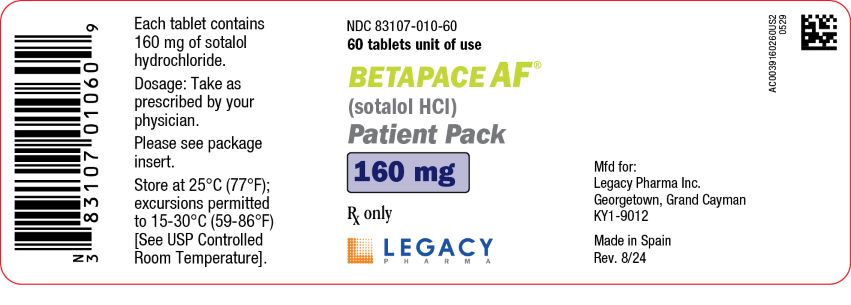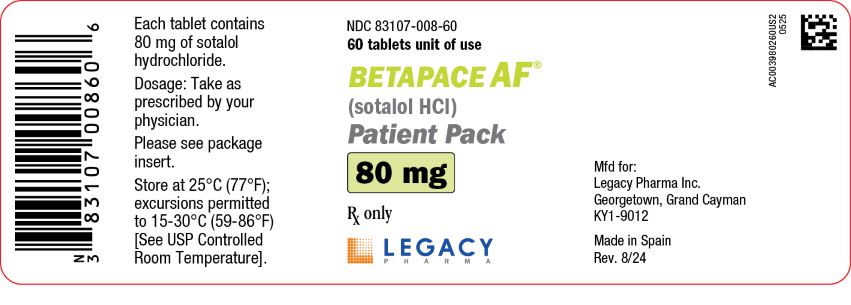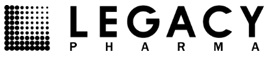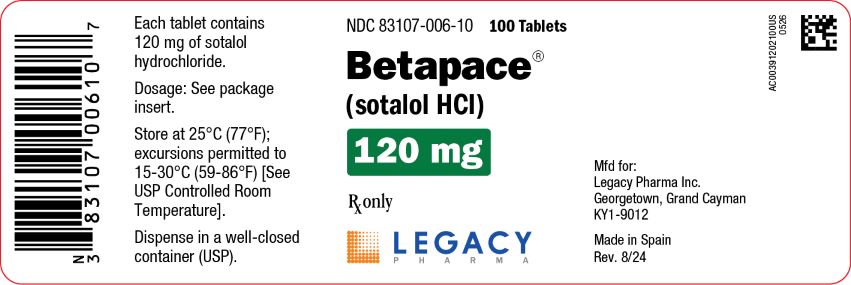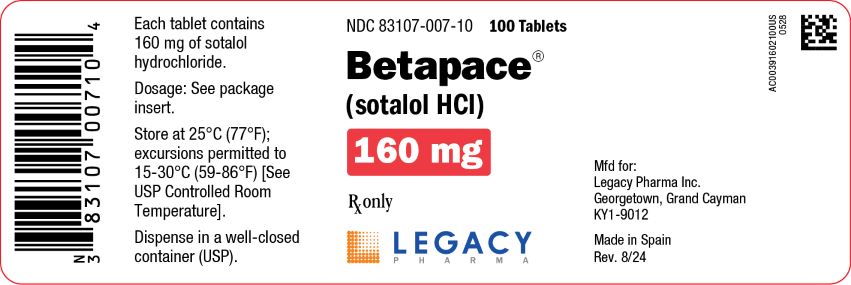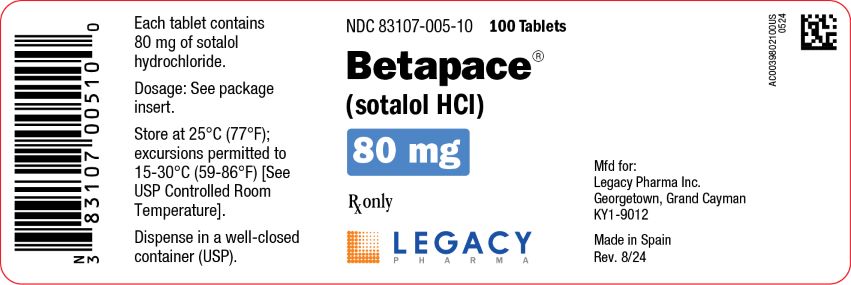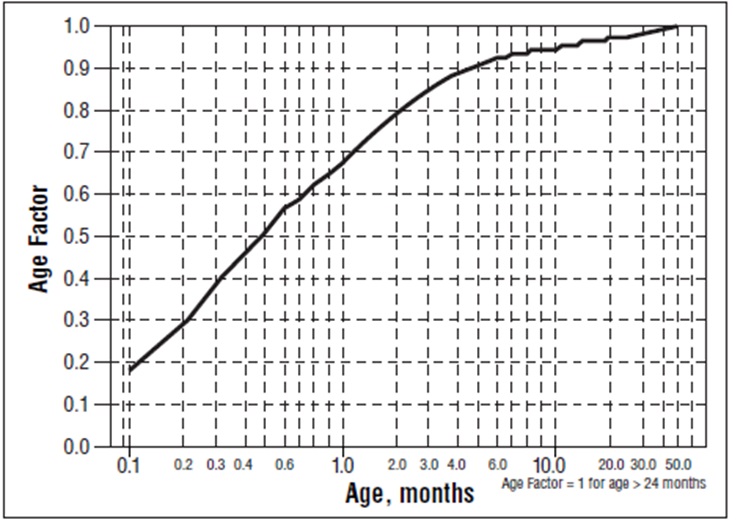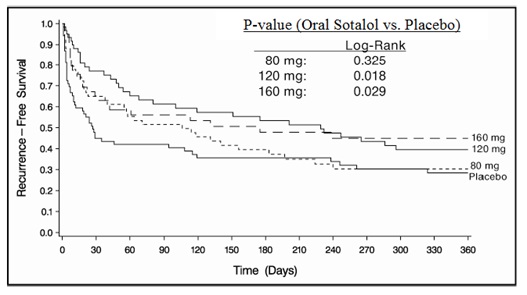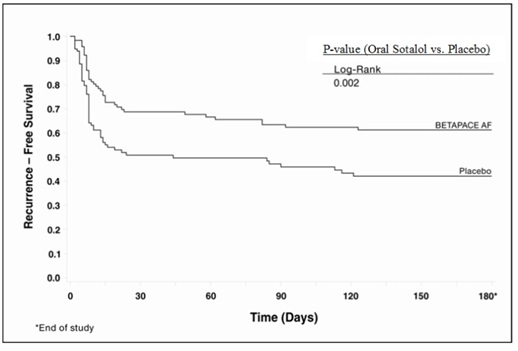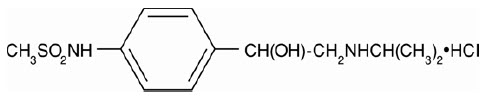 DRUG LABEL: BETAPACE
NDC: 83107-005 | Form: TABLET
Manufacturer: Legacy Pharma USA, Inc.
Category: prescription | Type: HUMAN PRESCRIPTION DRUG LABEL
Date: 20241216

ACTIVE INGREDIENTS: SOTALOL HYDROCHLORIDE 80 mg/1 1
INACTIVE INGREDIENTS: MICROCRYSTALLINE CELLULOSE; LACTOSE, UNSPECIFIED FORM; STARCH, CORN; STEARIC ACID; MAGNESIUM STEARATE; SILICON DIOXIDE; FD&C BLUE NO. 2

HIGHLIGHTS OF PRESCRIBING INFORMATION

These highlights do not include all the information needed to use BETAPACE®/BETAPACE AF safely and effectively. See full prescribing information for BETAPACE/BETAPACE AF.
BETAPACE (sotalol hydrochloride) tablets, for oral use
Initial U.S. Approval: 1992
BETAPACE AF (sotalol hydrochloride) tablets, for oral use
Initial U.S. Approval: 1992

WARNING: LIFE-THREATENING PROARRHYTHMIA

See full prescribing information for complete boxed warning.

- Betapace/Betapace AF can cause life-threatening ventricular tachycardia associated with QT interval prolongation.
- If the QT interval prolongs to 500 msec or greater, reduce the dose, lengthen the dosing interval, or discontinue the drug.
- Initiate or reinitiate in a facility that can provide cardiac resuscitation and continuous electrocardiographic monitoring.
- Adjust the dosing interval based on creatinine clearance.

1 INDICATIONS AND USAGE

Betapace/Betapace AF is an antiarrhythmic indicated for:

- the treatment of life-threatening ventricular arrhythmias (1.1)
- the maintenance of normal sinus rhythm in patients with atrial fibrillation or flutter (AFIB/AFL) (1.2)

Limitations of Use

- Betapace has not been shown to enhance survival in patients with life threatening ventricular arrhythmias (1.1)
- Avoid use in patients with minimally symptomatic or easily reversible AFIB/AFL (1.2)

2 DOSAGE AND ADMINISTRATION

- Betapace/Betapace AF: Initial dosage in adults is 80 mg twice daily. Increase the dose as needed in increments of 80 mg/day, every 3 days to a maximum 320 mg total daily dose (2.2)
- Pediatrics: Dosage depends on age (2.4)

3 DOSAGE FORMS AND STRENGTHS

80 mg, 120 mg, and 160 mg tablets (3)

4 CONTRAINDICATIONS

For the treatment of AFIB/AFL or ventricular arrhythmias

- Sinus bradycardia, 2nd or 3rd degree AV block, sick sinus syndrome (4)
- Congenital or acquired long QT syndrome (4)
- Serum potassium <4 mEq/L (4)
- Cardiogenic shock, decompensated heart failure (4)
- Bronchial asthma or related bronchospastic conditions (4)
- Hypersensitivity to sotalol (4)

For the treatment of AFIB/AFL also contraindicated for:

- QT interval >450 msec (4)

5 WARNINGS AND PRECAUTIONS

- QT prolongation, bradycardia, AV block, hypotension, worsening heart failure: Reduce dose or discontinue (5.1)
- Correct any electrolyte disturbances (5.1)
- Acute exacerbation of coronary artery disease upon cessation of therapy: Do not abruptly discontinue (5.5)
- Diabetes: May mask symptoms of hypoglycemia and alter glucose levels; monitor (5.7)

6 ADVERSE REACTIONS

The most common adverse reactions (≥2%) for Betapace are: fatigue 4%, bradycardia (less than 50 bpm) 3%, dyspnea 3%, proarrhythmia 3%, asthenia 2%, and dizziness 2%. (6)

To report SUSPECTED ADVERSE REACTIONS, contact Legacy Pharma Inc. at 1-800-727-7151 or FDA at 1-800-FDA-1088 or www.fda.gov/medwatch.

7 DRUG INTERACTIONS

- Class I or III Antiarrhythmics or other drugs that prolong the QT interval: Avoid concomitant use (7.1)
- Digoxin, calcium channel blocker: increased risk of bradycardia, hypotension, heart failure (7.2)
- Dosage of insulin or antidiabetic drugs may need adjustment (7.4)
- Aluminum- or magnesium-based antacids reduce sotalol exposure (7.7)

8 USE IN SPECIFIC POPULATIONS

- Lactation: Do not breastfeed (8.2)

FULL PRESCRIBING INFORMATION

WARNING: LIFE-THREATENING PROARRHYTHMIA

To minimize the risk of drug-induced arrhythmia, initiate or reinitiate oral sotalol in a facility that can provide cardiac resuscitation and continuous electrocardiographic monitoring.

Sotalol can cause life-threatening ventricular tachycardia associated with QT interval prolongation.

If the QT interval prolongs to 500 msec or greater, reduce the dose, lengthen the dosing interval, or discontinue the drug.

Calculate creatinine clearance to determine appropriate dosing [see Dosage and Administration (2.5)].

1 INDICATIONS AND USAGE

1.1 Life-Threatening Ventricular Arrhythmias

Betapace/Betapace AF is indicated for the treatment of documented, life-threatening ventricular arrhythmias, such as sustained ventricular tachycardia (VT).

Limitation of Use:

Betapace/Betapace AF has not been shown to enhance survival in patients with life-threatening ventricular arrhythmias.

1.2 Delay in Recurrence of Atrial Fibrillation/Atrial Flutter (AFIB/AFL)

Betapace/Betapace AF is indicated for the maintenance of normal sinus rhythm (delay in time to recurrence of AFIB/AFL) in patients with highly symptomatic AFIB/AFL who are currently in sinus rhythm.

Limitation of Use:

Because Betapace/Betapace AF can cause life-threatening ventricular arrhythmias, reserve its use for patients in whom AFIB/AFL is highly symptomatic. Patients with paroxysmal AFIB that is easily reversed (by Valsalva maneuver, for example) should usually not be given Betapace/Betapace AF.

2 DOSAGE AND ADMINISTRATION

2.1 General Safety Measures for Initiation of Oral Sotalol Therapy

Withdraw other antiarrhythmic therapy before starting Betapace/Betapace AF and monitor for a minimum of 2 to 3 plasma half-lives prior to initiating Betapace/Betapace AF therapy if the patient's clinical condition permits [see Drug Interactions (7)].

Hospitalize patients being initiated or re-initiated on sotalol for at least 3 days or until steady-state drug levels are achieved in a facility that can provide cardiac resuscitation and continuous electrocardiographic monitoring. Initiate oral sotalol therapy in the presence of personnel trained in the management of serious arrhythmias. Perform a baseline ECG to determine the QT interval and measure and normalize serum potassium and magnesium levels before initiating therapy. Measure serum creatinine and calculate an estimated creatinine clearance in order to establish the appropriate dosing interval. Monitor QTc 2 to 4 hours after each uptitration in dose.

Discharge patients on sotalol therapy from an in-patient setting with an adequate supply of sotalol to allow uninterrupted therapy until the patient can fill a sotalol prescription.

Advise patients who miss a dose to take the next dose at the usual time. Do not double the dose or shorten the dosing interval.

2.2 Adult Dose for Ventricular Arrhythmias

The recommended initial dose is 80 mg twice daily. This dose may be increased in increments of 80 mg per day every 3 days provided the QTc <500 msec [see Warnings and Precautions (5.1)]. Continually monitor patients until steady state blood levels are achieved. In most patients, a therapeutic response is obtained at a total daily dose of 160 to 320 mg/day, given in two or three divided doses. Oral doses as high as 480 to 640 mg/day have been utilized in patients with refractory life-threatening arrhythmias.

2.3 Adult Dose for Prevention of Recurrence of AFIB/AFL

The recommended initial dose is 80 mg twice daily. This dose may be increased in increments of 80 mg per day every 3 days provided the QTc <500 msec [see Warnings and Precautions (5.1)]. Continually monitor patients until steady state blood levels are achieved. Most patients will have satisfactory response with 120 mg twice daily. Initiation of sotalol in patients with QTc >450 msec is contraindicated [see Contraindications (4)].

2.4 Pediatric Dose for Ventricular Arrhythmias or AFIB/AFL

Use the same precautionary measures for children as you would use for adults when initiating and re-initiating sotalol treatment.

For Children Aged About 2 Years and Older

For children aged about 2 years and older with normal renal function, doses normalized for body surface area are appropriate for both initial and incremental dosing. Since the Class III potency in children is not very different from that in adults, reaching plasma concentrations that occur within the adult dose range is an appropriate guide [see Clinical Pharmacology (12.1, 12.3)].

For initiation of treatment, 1.2 mg/kg three times a day (3.6 mg/kg total daily dose) is approximately equivalent to the initial 160 mg total daily dose for adults. Subsequent titration to a maximum of 2.4 mg/kg three times a day (approximately equivalent to the 360 mg total daily dose for adults) can then occur. Titration should be guided by clinical response, heart rate, and QTc, with increased dosing being preferably conducted in-hospital. Allow at least 36 hours between dose increments to attain steady-state plasma concentrations of sotalol in patients with age‑adjusted normal renal function.

For Children Aged About 2 Years or Younger

For children aged about 2 years or younger, the pediatric dosage should be reduced by a factor that depends upon age, as shown in the following graph (age plotted on a logarithmic scale in months):

For a child aged 1 month, multiply the starting dose by 0.7; the initial starting dose would be (1.2 mg/kg X 0.7)=0.8 mg/kg, administered three times daily. For a child aged about 1 week, multiply the initial starting dose by 0.3; the starting dose would be (1.2 mg/kg X 0.3)=0.4 mg/kg. Use similar calculations for dose titration.

2.5 Dosage for Patients with Renal Impairment

Adults

In any age group with decreased renal function, sotalol doses should be lowered or the intervals between doses increased. It will take much longer to reach steady-state with any dose and/or frequency of administration. Closely monitor heart rate and QTc.

Dose escalations in renal impairment should be done after administration of at least 5 doses at appropriate intervals (Table 1). Sotalol is partly removed by dialysis; specific advice is unavailable on dosing patients on dialysis.

Administer the initial dose of 80 mg and subsequent doses at the intervals listed in Table 1.

Table 1: Dosing Intervals in Renal Impairment
Creatinine Clearance mL/min | Dosing Interval (hours)
>60 | 12
30–59 | 24
10–29 | 36–48
<10 | Dose should be individualized

2.6 Preparation of Extemporaneous Oral Solution

Betapace/Betapace AF Syrup 5 mg/mL can be compounded using Simple Syrup containing 0.1% sodium benzoate (Syrup, NF) as follows:

1. Measure 120 mL of Simple Syrup.
2. Transfer the syrup to a 6-ounce amber plastic (polyethylene terephthalate [PET]) prescription bottle. An oversized bottle is used to allow for a headspace, so that there will be more effective mixing during shaking of the bottle.
3. Add five (5) Betapace/Betapace AF 120 mg tablets to the bottle. These tablets are added intact; it is not necessary to crush the tablets. The addition of the tablets can also be done first. The tablets can also be crushed, if preferred. If the tablets are crushed, take care to transfer the entire quantity of tablet powder into the bottle containing the syrup.
4. Shake the bottle to wet the entire surface of the tablets. If the tablets have been crushed, shake the bottle until the endpoint is achieved.
5. Allow the tablets to hydrate for at least two hours.
6. After at least two hours have elapsed, shake the bottle intermittently over the course of at least another two hours until the tablets are completely disintegrated. The tablets can be allowed to hydrate overnight to simplify the disintegration process.

The endpoint is achieved when a dispersion of fine particles in the syrup is obtained.

This compounding procedure results in a solution containing 5 mg/mL of sotalol HCl. The fine solid particles are the water-insoluble inactive ingredients of the tablets.

Stability studies indicate that the suspension is stable for three months when stored at 15°C to 30°C (59°F to 86°F) [see USP Controlled Room Temperature] and ambient humidity.

3 DOSAGE FORMS AND STRENGTHS

Betapace is supplied as capsule-shaped, light-blue, scored tablets:

- 80 mg imprinted with “BETAPACE” on one side and 80 mg on the other
- 120 mg imprinted with “BETAPACE” on one side and 120 mg on the other
- 160 mg imprinted with “BETAPACE” on one side and 160 mg on the other

Betapace AF is supplied as capsule-shaped, white scored tablet:

- 80 mg imprinted with “BHCP” on one side and 80 mg on the other
- 120 mg imprinted with “BHCP” on one side and 120 mg on the other
- 160 mg imprinted with “BHCP” on one side and 160 mg on the other

4 CONTRAINDICATIONS

Betapace/Betapace AF is contraindicated in patients with:

- Sinus bradycardia, sick sinus syndrome, second and third degree AV block, unless a functioning pacemaker is present
- Congenital or acquired long QT syndromes
- Cardiogenic shock or decompensated heart failure
- Serum potassium <4 mEq/L
- Bronchial asthma or related bronchospastic conditions
- Hypersensitivity to sotalol

For the treatment of AFIB/AFL, Betapace/Betapace AF is also contraindicated in patients with:

- Baseline QT interval >450 msec

5 WARNINGS AND PRECAUTIONS

5.1 QT Prolongation and Proarrhythmia

Betapace/Betapace AF can cause serious and potentially fatal ventricular arrhythmias such as sustained VT/VF, primarily Torsade de Pointes (TdP) type ventricular tachycardia, a polymorphic ventricular tachycardia associated with QT interval prolongation. Factors such as reduced creatinine clearance, female sex, higher doses, reduced heart rate, and history of sustained VT/VF or heart failure increase the risk of TdP. The risk of TdP can be reduced by adjustment of the sotalol dose according to creatinine clearance and by monitoring the ECG for excessive increases in the QT interval [see Dosage and Administration (2.1)].

Correct hypokalemia or hypomagnesemia prior to initiating Betapace/Betapace AF, as these conditions can exaggerate the degree of QT prolongation, and increase the potential for Torsade de Pointes. Special attention should be given to electrolyte and acid-base balance in patients experiencing severe or prolonged diarrhea or patients receiving concomitant diuretic drugs.

Proarrhythmic events must be anticipated not only on initiating therapy, but with every upward dose adjustment [see Dosage and Administration (2.1)].

Avoid use with other drugs known to cause QT prolongation [see Drug Interactions (7.1)].

5.2 Bradycardia/Heart Block/Sick Sinus Syndrome

Sinus bradycardia (heart rate less than 50 bpm) occurred in 13% of patients receiving sotalol in clinical trials, and led to discontinuation in about 3% of patients. Bradycardia itself increases the risk of Torsade de Pointes. Sinus pause, sinus arrest and sinus node dysfunction occur in less than 1% of patients. The incidence of 2nd- or 3rd-degree AV block is approximately 1%.

Betapace/Betapace AF is contraindicated in patients with sick sinus syndrome because it may cause sinus bradycardia, sinus pauses, or sinus arrest.

5.3 Hypotension

Sotalol produces significant reductions in both systolic and diastolic blood pressures and may result in hypotension. Monitor hemodynamics in patients with marginal cardiac compensation.

5.4 Heart Failure

New onset or worsening heart failure may occur during initiation or uptitration of sotalol because of its beta-blocking effects. Monitor for signs and symptoms of heart failure and discontinue treatment if symptoms occur.

5.5 Cardiac Ischemia after Abrupt Discontinuation

Following abrupt cessation of therapy with beta-adrenergic blockers, exacerbations of angina pectoris and myocardial infarction may occur. When discontinuing chronically administered Betapace/Betapace AF, particularly in patients with ischemic heart disease, gradually reduce the dosage over a period of 1 to 2 weeks, if possible, and monitor the patient. If angina markedly worsens or acute coronary ischemia develops, treat appropriately and consider use of an alternative beta-blocker. Warn patients not to interrupt therapy without their physician’s advice. Because coronary artery disease is common, but may be unrecognized, the abrupt discontinuation of sotalol may unmask latent coronary insufficiency.

5.6 Bronchospasm

Patients with bronchospastic diseases (for example chronic bronchitis and emphysema) should not receive beta-blockers. If Betapace/Betapace AF is to be administered, use the smallest effective dose to minimize inhibition of bronchodilation produced by endogenous or exogenous catecholamine stimulation of beta-2-receptors.

5.7 Effects on Blood Sugar

Beta-blockers may prevent early warning signs of hypoglycemia, such as tachycardia, and increase the risk for severe or prolonged hypoglycemia at any time during treatment, especially in patients with diabetes mellitus or children and patients who are fasting (i.e., surgery, not eating regularly, or are vomiting). If severe hypoglycemia occurs, patients should be instructed to seek emergency treatment. Elevated blood glucose levels and increased insulin requirements can occur in diabetic patients.

5.8 Thyroid Abnormalities

Avoid abrupt withdrawal of beta-blockade in patients with thyroid disease because it may lead to an exacerbation of symptoms of hyperthyroidism, including thyroid storm. Beta-blockade may mask certain clinical signs (for example, tachycardia) of hyperthyroidism.

5.9 Anaphylaxis

While taking beta-blockers, patients with a history of anaphylactic reaction to a variety of allergens may have a more severe reaction on repeated challenge, either accidental, diagnostic, or therapeutic. Such patients may be unresponsive to the usual doses of epinephrine used to treat the allergic reaction.

5.10 Major Surgery

Chronically administered beta-blocking therapy should not be routinely withdrawn prior to major surgery; however, the impaired ability of the heart to respond to reflex adrenergic stimuli may augment the risks of general anesthesia and surgical procedures.

6 ADVERSE REACTIONS

6.1 Clinical Trials Experience

Because clinical trials are conducted under widely varying conditions, adverse reaction rates observed in the clinical trials of a drug cannot be directly compared to rates in the clinical trials of another drug and may not reflect the rates observed in practice.

Adverse reactions that are clearly related to sotalol are those which are typical of its Class II (beta-blocking) and Class III (cardiac action potential duration prolongation) effects and are dose related.

Ventricular Arrhythmias

Serious Adverse Reactions

Betapace/Betapace AF can cause serious and potentially fatal ventricular arrhythmias such as sustained VT/VF, primarily Torsade de Pointes (TdP) [see Warnings and Precautions (5.1)]. The effect on QT and the risk of Torsade de Pointes are both dose related.

Pediatric Patients

In an unblinded multicenter trial of 25 pediatric patients aged ≤ 1 month to 12 years with SVT and/or VT receiving daily doses of 30, 90, and 210 mg/m^2 with dosing every 8 hours for a total of 9 doses, no Torsade de Pointes or other serious new arrhythmias were observed. The clinical trial safety profile in pediatric patients was similar to that in adult patients. Both the Class III and beta-blocking effects of sotalol were linearly related to the plasma concentration [see Clinical Pharmacology (12.2)].

Atrial Fibrillation/Atrial Flutter

Placebo-controlled Clinical Trials

In a pooled clinical trial population consisting of 4 placebo-controlled studies with 275 patients with atrial fibrillation (AFIB)/atrial flutter (AFL) treated with 160 to 320 mg of Betapace AF, the following adverse reactions presented in Table 2 occurred in at least 2% of placebo-treated patients and at a lesser rate than Betapace-treated patients. The data are presented by incidence of reactions in the Betapace AF and placebo groups by body system and daily dose.

Table 2: Incidence (%) of Common Adverse Reactions (≥ 2% in the Placebo Group and Less Frequent Than in the Betapace AF Groups) in Four Placebo-controlled Studies of Patients with AFIB/AFL
Adverse Reaction | Placebo | Betapace AF Total Daily Dose
Adverse Reaction | N = 282 (%) | 160-240 mg N = 153 (%) | >240-320 mg N = 122 (%)
Bradycardia | 3 | 13 | 12
Diarrhea | 2 | 5 | 6
Nausea/Vomiting | 5 | 8 | 6
Fatigue | 9 | 20 | 19
Hyperhidrosis | 3 | 5 | 5
Weakness | 3 | 5 | 5
Dizziness | 12 | 16 | 13
Headache | 5 | 3 | 12
Dyspnea | 7 | 9 | 10

Overall, discontinuation because of unacceptable adverse events was necessary in 17% of the patients and occurred in 10% of patients less than two weeks after starting treatment. The most common adverse reactions leading to discontinuation of Betapace AF were: fatigue 4.6%, bradycardia 2.4%, proarrhythmia 2.2%, dyspnea 2%, and QT interval prolongation 1.4%.

6.2 Postmarketing Experience

The following adverse drug reactions have been identified during post-approval use of sotalol. Because these reactions are reported voluntarily from a population of uncertain size, it is not always possible to reliably estimate their frequency or establish a causal relationship to drug exposure: emotional lability, slightly clouded sensorium, incoordination, vertigo, paralysis, thrombocytopenia, eosinophilia, leukopenia, photosensitivity reaction, fever, pulmonary edema, hyperlipidemia, myalgia, pruritis, and alopecia.

7 DRUG INTERACTIONS

7.1 Antiarrhythmics and Other QT Prolonging Drugs

Discontinue Class I or Class III antiarrhythmic agents for at least three half-lives prior to dosing with sotalol. Class Ia antiarrhythmic drugs, such as disopyramide, quinidine, and procainamide, and other Class III drugs (for example, amiodarone) are not recommended as concomitant therapy with Betapace/Betapace AF, because of their potential to prolong refractoriness [see Warnings and Precautions (5.2)].

7.2 Negative Chronotropes

Digitalis glycosides, diltiazem, verapamil, and beta-blockers slow atrioventricular conduction and decrease heart rate. Concomitant use with negative chronotropes can increase the risk of bradycardia or hypotension.

7.3 Catecholamine-Depleting Agents

Concomitant use of catecholamine-depleting drugs, such as reserpine and guanethidine, with a beta-blocker may produce an excessive reduction of resting sympathetic nervous tone. Monitor such patients for evidence of hypotension and/or marked bradycardia which may produce syncope.

7.4 Insulin and Oral Antidiabetics

Hyperglycemia may occur, and the dosage of insulin or antidiabetic drugs may require adjustment [see Warnings and Precautions (5.7)].

7.5 Beta-2-Receptor Stimulants

Beta-agonists such as albuterol, terbutaline and isoproterenol may have to be administered in increased dosages when used concomitantly with sotalol.

7.6 Clonidine

Concomitant use with sotalol increases the risk of bradycardia and AV block. Because beta-blockers may potentiate the rebound hypertension sometimes observed after clonidine discontinuation, withdraw sotalol several days before the gradual withdrawal of clonidine to reduce the risk of rebound hypertension.

7.7 Antacids

Avoid administration of oral sotalol within 2 hours of antacids containing aluminum oxide and magnesium hydroxide.

7.8 Drug/Laboratory Test Interactions

The presence of sotalol in the urine may result in falsely elevated levels of urinary metanephrine when measured by fluorimetric or photometric methods.

8 USE IN SPECIFIC POPULATIONS

8.1 Pregnancy

Risk Summary

Both the untreated underlying condition in pregnancy and the use of sotalol in pregnancy cause adverse outcomes to the mother and fetus/neonate (see Clinical Considerations). In animal reproduction studies in rats, early resorptions were increased at 15 times the maximum recommended human dose (MRHD). In rabbits an increase in fetal death was observed at 2 times the MRHD administered as a single dose. Sotalol did not reveal any teratogenic potential in rats or rabbits at 15 and 2 times the MRHD respectively (see Data).

All pregnancies have a background risk of birth defect, loss, or other adverse outcomes. The estimated background risk of major birth defects and miscarriage for the indicated population is unknown. In the United States (U.S.) general population, the estimated background risk of major birth defects and miscarriage in clinically recognized pregnancies is 2% to 4% and 15% to 20%, respectively.

Clinical Considerations

The incidence of VT is increased and may be more symptomatic during pregnancy. Most tachycardia episodes are initiated by ectopic beats and the occurrence of arrhythmia episodes may, therefore, increase during pregnancy. Breakthrough arrhythmias may also occur during pregnancy, as therapeutic treatment levels may be difficult to maintain due to the increased volume of distribution and increased drug metabolism inherent in the pregnant state.

Fetal/Neonatal Adverse Reactions

Sotalol has been shown to cross the placenta and is found in amniotic fluid. From published observational studies, the potential fetal adverse effects of sotalol use during pregnancy are growth restriction, transient fetal bradycardia, hyperbilirubinemia, hypoglycemia, uterine contractions, and possible intrauterine death. Sotalol may have a greater effect on QT prolongation in the immature heart than in the adult heart, and therefore, conveys an increased risk of serious fetal arrhythmia and/or possible intrauterine death. Monitor the newborn for symptoms of beta blockade.

Labor or Delivery

Generally, risk of arrhythmias increases during the labor and delivery process; therefore, considering the proarrhythmia potential of the drug, patients treated with sotalol should be monitored continuously during labor and delivery.

Data

Animal Data

Reproduction studies in rats and rabbits administered sotalol during organogenesis at 15 times and 2 times the MRHD as mg/m^2, respectively, did not reveal any teratogenic potential associated with sotalol.

In pregnant rats, sotalol doses administered during organogenesis at approximately 15 times the MRHD as mg/m^2, increased the number of early resorptions, while no increase in early resorptions was noted at 2 times the MRHD as mg/m^2.

In reproductive studies in rabbits, a sotalol dose (160 mg/kg/day) at 5 times the MRHD as mg/m^2 produced a slight increase in fetal death, and maternal toxicity. However, one study from published data reported an increase in fetal deaths in rabbits receiving a single dose (50 mg/kg) at 2 times the MRHD as mg/m^2 on gestation day 14.

8.2 Lactation

Risk Summary

Limited available data from published literature report that sotalol is present in human milk. The estimated daily infant dose of sotalol received from breastmilk is 0.8-3.4 mg/kg, estimated at 22 to 25.5% of the maternal weight-adjusted dosage of Betapace (see Data). The amount of the drug in breast milk is similar to the neonatal therapeutic dosage. Therefore, there is potential for bradycardia and other symptoms of beta blockade such as dry mouth, skin or eyes, diarrhea or constipation in the breastfed infant. There is no information regarding the effects of sotalol on milk production. Because of the potential serious adverse reactions to the breastfed child and the high level of sotalol in breast milk, advise women not to breastfeed while on treatment with Betapace.

Data

Sotalol is present in human milk in high levels. A prospective study evaluated 20 paired samples of breast milk and maternal blood from 5 mothers who elected to breastfeed. Breast milk samples had a mean sotalol concentration of 10.5 µg/mL (± 1.1 µg/mL; range: 4.8 to 20.2 µg/mL) compared to a simultaneous mean maternal plasma concentration of 2.3 µg/mL (± 0.3 µg/mL; range: 0.8 to 5.0 µg/mL). The mean milk plasma ratio was 5.4:1 (range: 2.2 to 8.8). The estimated daily infant dose was 0.8-3.4 mg/kg, estimated at 22 to 25.5% of the maternal weight-adjusted dosage of sotalol. This is similar to recommended therapeutic dose in neonates. None of the mothers reported any adverse reactions in the breastfed infant.

8.3 Females and Males of Reproductive Potential

Infertility

Based on the published literature, beta blockers (including sotalol) may cause erectile dysfunction.

8.4 Pediatric Use

The safety and effectiveness of sotalol in children have not been established. However, the Class III electrophysiologic and beta-blocking effects, the pharmacokinetics, and the relationship between the effects (QTc interval and resting heart rate) and drug concentrations have been evaluated in children aged between 3 days and 12 years old [see Dosage and Administration (2.4) and Clinical Pharmacology (12.2)].

Associated side effects of sotalol use in pediatric patients are those typical of a beta-blocking agent, and lead to discontinuation of the drug in 3 to 6% of patients. As in adults, the Class III antiarrhythmic action of sotalol in pediatric patients is associated with a significant proarrhythmic potential for adverse effects. In pediatric patients, the incidence of proarrhythmic side effects of sotalol varies from 0 to 22%; however, sotalol-induced Torsade de Pointes tachycardias are observed less frequently in the pediatric population.

Proarrhythmic effects of sotalol in pediatric patients included increased ventricular ectopy and exacerbation of bradycardia, the latter predominantly in patients with sinus node dysfunction following surgery for congenital cardiac defects. Bradycardia may require emergency pacemaker implantation. Close in-patient monitoring is recommended for several days.

8.6 Renal Impairment

Sotalol is mainly eliminated via the kidneys. Adjust dosing intervals based on creatinine clearance [see Dosage and Administration (2.5)].

10 OVERDOSAGE

Intentional or accidental overdosage with sotalol has resulted in death.

Symptoms and Treatment of Overdosage

The most common signs to be expected are bradycardia, congestive heart failure, hypotension, bronchospasm, and hypoglycemia. In cases of massive intentional overdosage (2 to 16 grams) of sotalol the following clinical findings were seen: hypotension, bradycardia, cardiac asystole, prolongation of QT interval, Torsade de Pointes, ventricular tachycardia, and premature ventricular complexes. If overdosage occurs, therapy with sotalol should be discontinued and the patient observed closely. Because of the lack of protein binding, hemodialysis is useful for reducing sotalol plasma concentrations. Patients should be carefully observed until QT intervals are normalized and the heart rate returns to levels >50 bpm.

The occurrence of hypotension following an overdose may be associated with an initial slow drug elimination phase (half-life of 30 hours) thought to be due to a temporary reduction of renal function caused by the hypotension. In addition, if required, the following therapeutic measures are suggested:

Bradycardia or Cardiac Asystole: Atropine, another anticholinergic drug, a beta-adrenergic agonist, or transvenous cardiac pacing.

Heart Block: (second and third degree) transvenous cardiac pacemaker.

Hypotension: (depending on associated factors) epinephrine rather than isoproterenol or norepinephrine may be useful.

Bronchospasm: Aminophylline or aerosol beta-2-receptor stimulant. Higher than normal doses of beta-2-receptor stimulants may be required.

Torsade de Pointes: DC cardioversion, transvenous cardiac pacing, epinephrine, magnesium sulfate.

11 DESCRIPTION

Betapace/Betapace AF contains sotalol hydrochloride, an antiarrhythmic drug with Class II (beta-adrenoreceptor blocking) and Class III (cardiac action potential duration prolongation) properties. Betapace is supplied as a light-blue, capsule-shaped tablet for oral administration. Betapace AF is supplied as a white, capsule-shaped tablet for oral administration. Sotalol hydrochloride is a white, crystalline solid with a molecular weight of 308.8. It is hydrophilic, soluble in water, propylene glycol, and ethanol, but is only slightly soluble in chloroform. Chemically, sotalol hydrochloride is d,l-N-[4-[1-hydroxy-2-[(1-methylethyl) amino]ethyl]phenyl]methane-sulfonamide monohydrochloride. The molecular formula is C12H20N2O3 S∙HCl and is represented by the following structural formula:

Betapace Tablets contain the following inactive ingredients: microcrystalline cellulose, lactose, starch, stearic acid, magnesium stearate, colloidal silicon dioxide, and FD&C blue color #2 (aluminum lake, conc.).

Betapace AF Tablets contain the following inactive ingredients: microcrystalline cellulose, lactose, starch, stearic acid, magnesium stearate, and colloidal silicon dioxide.

12 CLINICAL PHARMACOLOGY

12.1 Mechanism of Action

Sotalol has both beta-adrenoreceptor blocking (Vaughan Williams Class II) and cardiac action potential duration prolongation (Vaughan Williams Class III) antiarrhythmic properties. The two isomers of sotalol have similar Class III antiarrhythmic effects, while the l-isomer is responsible for virtually all of the beta-blocking activity. The beta-blocking effect of sotalol is non-cardioselective, half maximal at about 80 mg/day and maximal at doses between 320 and 640 mg/day. Sotalol does not have partial agonist or membrane stabilizing activity. Although significant beta-blockade occurs at oral doses as low as 25 mg, significant Class III effects are seen only at daily doses of 160 mg and above.

In children, a Class III electrophysiologic effect can be seen at daily doses of 210 mg/m^2 body surface area (BSA). A reduction of the resting heart rate due to the beta-blocking effect of sotalol is observed at daily doses ≥90 mg/m^2 in children.

12.2 Pharmacodynamics

Cardiac Electrophysiological Effects

Sotalol hydrochloride prolongs the plateau phase of the cardiac action potential in the isolated myocyte, as well as in isolated tissue preparations of ventricular or atrial muscle (Class III activity). In intact animals it slows heart rate, decreases AV nodal conduction, and increases the refractory periods of atrial and ventricular muscle and conduction tissue.

In man, the Class II (beta-blockade) electrophysiological effects of sotalol are manifested by increased sinus cycle length (slowed heart rate), decreased AV nodal conduction and increased AV nodal refractoriness. The Class III electrophysiological effects in man include prolongation of the atrial and ventricular monophasic action potentials, and effective refractory period prolongation of atrial muscle, ventricular muscle, and atrio-ventricular accessory pathways (where present) in both the anterograde and retrograde directions. With oral doses of 160 to 640 mg/day, the surface ECG shows dose-related mean increases of 40 to 100 msec in QT and 10 to 40 msec in QTc [see Warnings and Precautions (5.1)]. No significant alteration in QRS interval is observed.

In a small study (n=25) of patients with implanted defibrillators treated concurrently with Betapace, the average defibrillatory threshold was 6 joules (range: 2 to 15 joules) compared to a mean of 16 joules for a nonrandomized comparative group primarily receiving amiodarone.

Twenty-five children in an unblinded, multicenter trial with SVT and/or ventricular tachyarrhythmias, aged between 3 days and 12 years (mostly neonates and infants), received an ascending titration regimen with daily doses of 30, 90, and 210 mg/m^2 with dosing every 8 hours for a total 9 doses. During steady-state, the respective average increases above baseline of the QTc interval were 2, 14, and 29 msec at the 3 dose levels. The respective mean maximum increases above baseline of the QTc interval were 23, 36, and 55 msec at the 3 dose levels. The steady-state percent increases in the RR interval were 3, 9, and 12%. The smallest children (BSA <0.33 m^2) showed a tendency for larger Class III effects (ΔQTc) and an increased frequency of prolongations of the QTc interval as compared with larger children (BSA ≥0.33 m^2). The beta-blocking effects also tended to be greater in the smaller children (BSA <0.33 m^2). Both the Class III and beta-blocking effects of sotalol were linearly related to the plasma concentrations.

Hemodynamics

In a study of systemic hemodynamic function measured invasively in 12 patients with a mean LV ejection fraction of 37% and ventricular tachycardia (9 sustained and 3 non-sustained), a median dose of 160 mg twice daily of Betapace produced a 28% reduction in heart rate and a 24% decrease in cardiac index at 2 hours post-dosing at steady-state. Concurrently, systemic vascular resistance and stroke volume showed nonsignificant increases of 25% and 8%, respectively. One patient was discontinued because of worsening congestive heart failure. Pulmonary capillary wedge pressure increased significantly from 6.4 to 11.8 mmHg in the 11 patients who completed the study. Mean arterial pressure, mean pulmonary artery pressure and stroke work index did not significantly change. Exercise and isoproterenol induced tachycardia are antagonized by Betapace, and total peripheral resistance increases by a small amount.

In hypertensive patients, sotalol produces significant reductions in both systolic and diastolic blood pressures. Although sotalol is usually well-tolerated hemodynamically, deterioration in cardiac performance may occur in patients with marginal cardiac compensation [see Warnings and Precautions (5.3)].

12.3 Pharmacokinetics

The pharmacokinetics of the d- and l-enantiomers of sotalol are essentially identical.

Absorption

In healthy subjects, the oral bioavailability of sotalol is 90 to 100%. After oral administration, peak plasma concentrations are reached in 2.5 to 4 hours, and steady-state plasma concentrations are attained within 2 to 3 days (that is, after 5 to 6 doses when administered twice daily). Over the dosage range 160 to 640 mg/day, sotalol displays dose proportionality with respect to plasma concentrations. When administered with a standard meal, the absorption of sotalol was reduced by approximately 20% compared to administration in fasting state.

Distribution

Sotalol does not bind to plasma proteins. Distribution occurs to a central (plasma) and to a peripheral compartment. Sotalol crosses the blood brain barrier poorly.

Metabolism

Sotalol is not metabolized and is not expected to inhibit or induce any CYP450 enzymes.

Excretion

Excretion of sotalol is predominantly via the kidney in the unchanged form, and therefore, lower doses are necessary in conditions of renal impairment [see Dosage and Administration (2.5)]. The mean elimination half-life of sotalol is 12 hours. Dosing every 12 hours results in trough plasma concentrations which are approximately one-half of those at peak.

Specific Populations

Pediatric: The combined analysis of a single-dose study and a multiple-dose study with 59 children, aged between 3 days and 12 years, showed the pharmacokinetics of sotalol to be first order. A daily dose of 30 mg/m^2 of sotalol was administered in the single dose study and daily doses of 30, 90, and 210 mg/m^2 were administered every 8 hours in the multidose study. After rapid absorption with peak levels occurring on average between 2 to 3 hours following administration, sotalol was eliminated with a mean half-life of 9.5 hours. Steady-state was reached after 1 to 2 days. The average peak to trough concentration ratio was 2. Body surface area was the most important covariate and more relevant than age for the pharmacokinetics of sotalol. The smallest children (BSA <0.33 m^2) exhibited a greater drug exposure (+59%) than the larger children who showed a uniform drug concentration profile. The intersubject variation for oral clearance was 22%.

Geriatric: Age does not significantly alter the pharmacokinetics of Betapace/Betapace AF, but impaired renal function in geriatric patients can increase the terminal elimination half-life, resulting in increased drug accumulation.

Renal Impairment: Sotalol is mainly eliminated via the kidneys through glomerular filtration and to a small degree by tubular secretion. There is a direct relationship between renal function, as measured by serum creatinine or creatinine clearance, and the elimination rate of sotalol. The half-life of sotalol is prolonged (up to 69 hours) in anuric patients. Adjust doses or dosing intervals based on creatinine clearance [see Dosage and Administration (2.5)].

Hepatic Impairment: Patients with hepatic impairment show no alteration in clearance of sotalol.

Drug-Drug Interactions

Antacids: Administration of oral sotalol within 2 hours of antacids may result in a reduction in Cmax and AUC of 26% and 20%, respectively, and consequently in a 25% reduction in the bradycardic effect at rest. Administration of the antacid two hours after oral sotalol has no effect on the pharmacokinetics or pharmacodynamics of sotalol.

No pharmacokinetic interactions were observed with hydrochlorothiazide or warfarin.

13 NONCLINICAL TOXICOLOGY

13.1 Carcinogenesis, Mutagenesis, Impairment of Fertility

Calculations of safety margins are for the maximum recommended human dose (MRHD) of 640 mg/day of sotalol, administered for life-threatening ventricular arrhythmias in a 60-kg human.

No evidence of carcinogenic potential was observed in rats during a 24-month study at 137 to 275 mg/kg/day (approximately 30 times the maximum recommended human oral dose (MRHD) as mg/kg or 5 times the MRHD as mg/m^2) or in mice, during a 24-month study at 4141 to 7122 mg/kg/day (approximately 450 to 750 times the MRHD as mg/kg or 36 to 63 times the MRHD as mg/m^2).

Sotalol has not been evaluated in any specific assay of mutagenicity or clastogenicity.

13.2 Animal Toxicology and/or Pharmacology

No significant reduction in fertility occurred in rats at oral doses of 1000 mg/kg/day (approximately 94 times the MRHD as mg/kg or 15 times the MRHD as mg/m^2) prior to mating, except for a small reduction in the number of offspring per litter.

14 CLINICAL STUDIES

14.1 Ventricular Arrhythmias

In patients with life-threatening arrhythmias [sustained ventricular tachycardia/fibrillation (VT/VF)], Betapace was studied acutely [by suppression of programmed electrical stimulation (PES) induced VT and by suppression of Holter monitor evidence of sustained VT] and, in acute responders, chronically.

In a double-blind, randomized comparison of Betapace and procainamide in 104 patients given intravenously (total of 2 mg/kg Betapace vs. 19 mg/kg of procainamide over 90 minutes), Betapace suppressed PES induction in 30% of patients vs. 20% for procainamide (P=0.2).

In a randomized clinical trial (Electrophysiologic Study Versus Electrocardiographic Monitoring [ESVEM] Trial) in 486 patients comparing the choice of antiarrhythmic therapy by PES suppression vs. Holter monitor selection (in each case followed by treadmill exercise testing) in patients with a history of sustained VT/VF who were also inducible by PES, the effectiveness acutely and chronically of Betapace was compared with that of 6 other drugs (procainamide, quinidine, mexiletine, propafenone, imipramine, and pirmenol). The Overall response, limited to first randomized drug, was 39% for Betapace and 30% for the pooled other drugs. Acute response rate for first drug randomized using suppression of PES induction was 36% for Betapace vs. a mean of 13% for the pooled other drugs. Using the Holter monitoring endpoint (complete suppression of sustained VT, 90% suppression of NSVT, 80% suppression of PVC pairs, and at least 70% suppression of PVCs), Betapace yielded 41% response vs. 45% for the other drugs combined. Among responders placed on long-term therapy identified acutely as effective (by either PES or Holter), Betapace, when compared to the pool of other drugs, had the lowest two-year mortality (13% vs. 22%), the lowest two-year VT recurrence rate (30% vs. 60%), and the lowest withdrawal rate (38% vs. about 75 to 80%). The most commonly used doses of orally administered Betapace in this trial were 320 to 480 mg/day (66% of patients), with 16% receiving 240 mg/day or less and 18% receiving 640 mg or more.

It cannot be determined, however, in the absence of a controlled comparison of Betapace vs. no pharmacologic treatment (for example, in patients with implanted defibrillators) whether Betapace response causes improved survival or identifies a population with a good prognosis.

Betapace has not been shown to enhance survival in patients with ventricular arrhythmias.

14.2 Supraventricular Arrhythmias

Betapace AF has been studied in patients with symptomatic AFIB/AFL in two principal studies, one in patients with primarily paroxysmal AFIB/AFL, the other in patients with primarily chronic AFIB.

In one study, a U.S. multicenter, randomized, placebo-controlled, double-blind, dose-response trial of patients with symptomatic primarily paroxysmal AFIB/AFL, three fixed dose levels of Betapace AF (80 mg, 120 mg, and 160 mg) twice daily and placebo were compared in 253 patients. In patients with reduced creatinine clearance (40 to 60 mL/min) the same doses were given once daily. Patients were excluded for the following reasons: QT >450 msec; creatinine clearance <40 mL/min; intolerance to beta-blockers; bradycardia-tachycardia syndrome in the absence of an implanted pacemaker; AFIB/AFL was asymptomatic or was associated with syncope, embolic CVA or TIA; acute myocardial infarction within the previous 2 months; congestive heart failure; bronchial asthma or other contraindications to beta-blocker therapy; receiving potassium-losing diuretics without potassium replacement or without concurrent use of ACE-inhibitors; uncorrected hypokalemia (serum potassium <3.5 MEq/L) or hypomagnesemia (serum magnesium <1.5 MEq/L); received chronic oral amiodarone therapy for >1 month within previous 12 weeks; congenital or acquired long QT syndromes; history of Torsade de Pointes with other antiarrhythmic agents, which increase the duration of ventricular repolarization; sinus rate <50 bpm during waking hours; unstable angina pectoris; receiving treatment with other drugs that prolong the QT interval; and AFIB/AFL associated with the Wolff-Parkinson-White (WPW) syndrome. If the QT interval increased to ≥520 msec (or JT ≥430 msec if QRS >100 msec) the drug was discontinued. The patient population in this trial was 64% male, and the mean age was 62 years. No structural heart disease was present in 43% of the patients. Doses were administered once daily in 20% of the patients because of reduced creatinine clearance.

Betapace AF was shown to prolong the time to the first symptomatic, ECG-documented recurrence of AFIB/AFL, as well as to reduce the risk of such recurrences at both 6 and 12 months. The 120 mg dose was more effective than 80 mg, but 160 mg did not appear to have an added benefit. Note that these doses were given twice or once daily, depending on renal function. The results are shown in Figure 1,Table 3, and Table 4.

Figure 1: Study 1 – Time to First ECG-Documented Recurrence of Symptomatic AFIB/AFL Since Randomization

Table 3: Study 1 - Patient Status at 12 Months

 | Placebo | Betapace AF Dose
 | Placebo | 80 mg | 120 mg | 160 mg
Randomized | 69 | 59 | 63 | 62
On treatment in NSR at 12 months without recurrencea | 23% | 22% | 29% | 23%
Recurrenceab | 67% | 58% | 49% | 42%
D/C for AEs | 6% | 12% | 18% | 29%
a Symptomatic AFIB/AFL
b Efficacy endpoint of Study 1; study treatment stopped.

Note that columns do not add up to 100% due to discontinuations (D/C) for “other” reasons.

Table 4: Study 1 - Median Time to Recurrence of Symptomatic AFIB/AFL and Relative Risk (vs. Placebo) at 12 Months
 | Placebo n=69 | Betapace AF Dose
 | Placebo n=69 | 80 mg n=59 | 120 mg n=63 | 160 mg n=62
P-value vs. placebo |  | 0.325 | 0.018 | 0.029
Relative Risk (RR) to placebo |  | 0.81 | 0.59 | 0.59
Median time to recurrence (days) | 27 | 106 | 229 | 175

Discontinuation because of adverse events was dose-related.

In a second multicenter, randomized, placebo-controlled, double-blind study of 6 months duration in 232 patients with chronic AFIB, Betapace AF was titrated over a dose range from 80 mg/day to 320 mg/day. The patient population of this trial was 70% male with a mean age of 65 years. Structural heart disease was present in 49% of the patients. All patients had chronic AFIB for >2 weeks but <1 year at entry with a mean duration of 4.1 months. Patients were excluded if they had significant electrolyte imbalance, QTc >460 msec, QRS >140 msec, any degree of AV block or functioning pacemaker, uncompensated cardiac failure, asthma, significant renal disease (estimated creatinine clearance <50 mL/min), heart rate <50 bpm, myocardial infarction or open heart surgery in past 2 months, unstable angina, infective endocarditis, active pericarditis or myocarditis, ≥3 DC cardioversions in the past, medications that prolonged QT interval, and previous amiodarone treatment.

After successful cardioversion patients were randomized to receive placebo (n=114) or Betapace AF (n=118) at a starting dose of 80 mg twice daily. If the initial dose was not tolerated it was decreased to 80 mg once daily, but if it was tolerated, it was increased to 160 mg twice daily. During the maintenance period 67% of treated patients received a dose of 160 mg twice daily, and the remainder received doses of 80 mg once daily (17%) and 80 mg twice daily (16%).

Tables 5 and 6 show the results of the trial. There was a longer time to ECG-documented recurrence of AFIB and a reduced risk of recurrence at 6 months compared to placebo.

Table 5: Study 2 - Patient Status at 6 Months
 | Placebo n=114 | Betapace AF n=118
On treatment in NSR at 6 months without recurrencea | 29% | 45%
Recurrenceab | 67% | 49%
D/C for AEs | 3% | 6%
Death | 1%
a Symptomatic or asymptomatic AFIB/AFL
b Efficacy endpoint of Study 2; study treatment stopped.

Table 6: Study 2 - Median Time to Recurrence of Symptomatic AFIB/AFL/Death and Relative Risk (vs. Placebo) at 6 Months
 | Placebo n=114 | Betapace AF n=118 | Relative Risk | P-value
Median time to recurrence (days) | 44 | >180 | 0.55 | 0.002

Figure 2: Study 2 – Time to First ECG-Documented Recurrence of Symptomatic AFIB/AFL/Death Since Randomization

16 HOW SUPPLIED/STORAGE AND HANDLING

Betapace (sotalol hydrochloride); capsule-shaped light-blue scored tablets, imprinted with the strength and “BETAPACE,” are available as follows:

NDC 83107-005-10 80 mg strength, bottle of 100
NDC 83107-006-10 120 mg strength, bottle of 100
NDC 83107-007-10 160 mg strength, bottle of 100

Betapace AF (sotalol hydrochloride); capsule-shaped white scored tablets, imprinted with the strength and “BHCP” are available as follows:

NDC 83107-008-60 80 mg strength, bottle of 60
NDC 83107-009-60 120 mg strength, bottle of 60
NDC 83107-010-60 160 mg strength, bottle of 60

Store at 25°C (77°F); excursions permitted to 15 to 30°C (59 to 86°F) [see USP Controlled Room Temperature].

17 PATIENT COUNSELING INFORMATION

- Advise patients to contact their healthcare provider in the event of syncope, pre-syncopal symptoms or cardiac palpitations.
- Advise patients that their electrolytes and ECG will be monitored during treatment [see Warnings and Precautions (5.1)].
- Advise patients to contact their healthcare provider in the event of conditions that could lead to electrolyte changes such as severe diarrhea, unusual sweating, vomiting, less appetite than normal, or excessive thirst [see Warnings and Precautions (5.1)].
- Advise patients not to change the Betapace/Betapace AF dose prescribed by their healthcare provider.
- Advise patients that they should not miss a dose, but if they do miss a dose they should not double the next dose to compensate for the missed dose: they should take the next dose at the regularly scheduled time [see Dosage and Administration (2)].
- Advise patients to not interrupt or discontinue Betapace/Betapace AF without their physician’s advice, that they should get their prescription for sotalol filled and refilled on time, so they do not interrupt treatment [see Dosage and Administration (2)].
- Advise patients to not start taking other medications without first discussing new medications with their healthcare provider.
- Advise patients to avoid taking Betapace/Betapace AF within two hours of taking antacids that contain aluminum oxide or magnesium hydroxide [see Drug Interactions (7.7)].
- Inform patients or caregivers that there is a risk of hypoglycemia when Betapace/Betapace AF is given to patients who are fasting or who are vomiting. Inform patients to notify their healthcare provider if they experience symptoms of hypoglycemia. [See Warnings and Precautions (5.7)].

Lactation

- Advise women not to breastfeed while on treatment with Betapace [see Use in Specific Populations (8.2)].

©2023, Legacy Pharma Inc. All rights reserved.

Manufactured for:

Legacy Pharma Inc.
St. Michael, Barbados
BB14017

PRINCIPAL DISPLAY PANEL - 80 mg BETAPACE

NDC 83107-005-10 100 Tablets

Betapace®
(sotalol HCl)

80 mg

Rx only

LEGACY
PHARMA

Each tablet contains
80 mg of sotalol
hydrochloride.

Dosage: See package
insert.

Store at 25°C (77°F);
excursions permitted
to 15-30°C (59-86°F)
[See USP Controlled
Room Temperature].

Dispense in a
well-closed
container (USP).

Mfd for:
Legacy Pharma Inc.
Georgetown, Grand Cayman
KY1-9012

Made in Spain

Rev. 8/24

PRINCIPAL DISPLAY PANEL - 120 mg BETAPACE

NDC 83107-006-10
100 Tablets

Betapace®
(sotalol HCl)

120 mg

Rx only

LEGACY
PHARMA

Each tablet
contains 120 mg
of sotalol
hydrochloride.

Dosage: See
package insert.

Store at 25°C
(77°F); excursions
permitted to
15-30°C (59-86°F)
[See USP
Controlled Room
Temperature].

Dispense in a
well-closed
container (USP).

Mfd for:
Legacy Pharma Inc.
Georgetown, Grand Cayman
KY1-9012

Made in Spain

Rev. 8/24

PRINCIPAL DISPLAY PANEL - 160 mg BETAPACE

NDC 83107-007-10
100 Tablets

Betapace®
(sotalol HCl)

160 mg

Rx only

LEGACY
PHARMA

Each tablet
contains 160 mg
of sotalol
hydrochloride.

Dosage: See
package insert.

Store at 25°C
(77°F); excursions
permitted to
15-30°C
(59-86°F) [See
USP Controlled
Room
Temperature].

Dispense in a
well-closed
container (USP).

Mfd for:
Legacy Pharma Inc.
Georgetown, Grand Cayman
KY1-9012

Made in Spain

Rev. 8/24

PRINCIPAL DISPLAY PANEL - 80 mg BETAPACE AF

NDC 83107-008-60
60 tablets unit of use

BETAPACE AF®
(sotalol HCl)
Patient Pack

80 mg

Rx only

LEGACY
PHARMA

Each tablet
contains 80 mg
of sotalol
hydrochloride.

Dosage: Take as
prescribed by your
physician.

Please see
package insert.

Store at 25°C
(77°F); excursions
permitted to
15-30°C (59-86°F)
[See USP
Controlled Room
Temperature].

Mfd for:
Legacy Pharma Inc.
Georgetown, Grand Cayman
KY1-9012

Made in Spain

Rev. 8/24

PRINCIPAL DISPLAY PANEL - 120 mg BETAPACE AF

NDC 83107-009-60
60 tablets unit of use

BETAPACE AF®
(sotalol HCl)
Patient Pack

120 mg

Rx only

LEGACY
PHARMA

Each tablet
contains 120 mg
of sotalol
hydrochloride.

Dosage: Take as
prescribed by your
physician.

Please see
package insert.

Store at 25°C
(77°F); excursions
permitted to
15-30°C (59-86°F)
[See USP
Controlled Room
Temperature].

Mfd for:
Legacy Pharma Inc.
Georgetown, Grand Cayman
KY1-9012

Made in Spain

Rev. 8/24

PRINCIPAL DISPLAY PANEL - 160 mg BETAPACE AF

NDC 83107-010-60
60 tablets unit of use

BETAPACE AF®
(sotalol HCl)
Patient Pack

160 mg

Rx only

LEGACY
PHARMA

Each tablet
contains 160 mg
of sotalol
hydrochloride.

Dosage: Take as
prescribed by your
physician.

Please see
package insert.

Store at 25°C
(77°F); excursions
permitted to
15-30°C (59-86°F)
[See USP
Controlled Room
Temperature].

Mfd for:
Legacy Pharma Inc.
Georgetown, Grand Cayman
KY1-9012

Made in Spain

Rev. 8/24